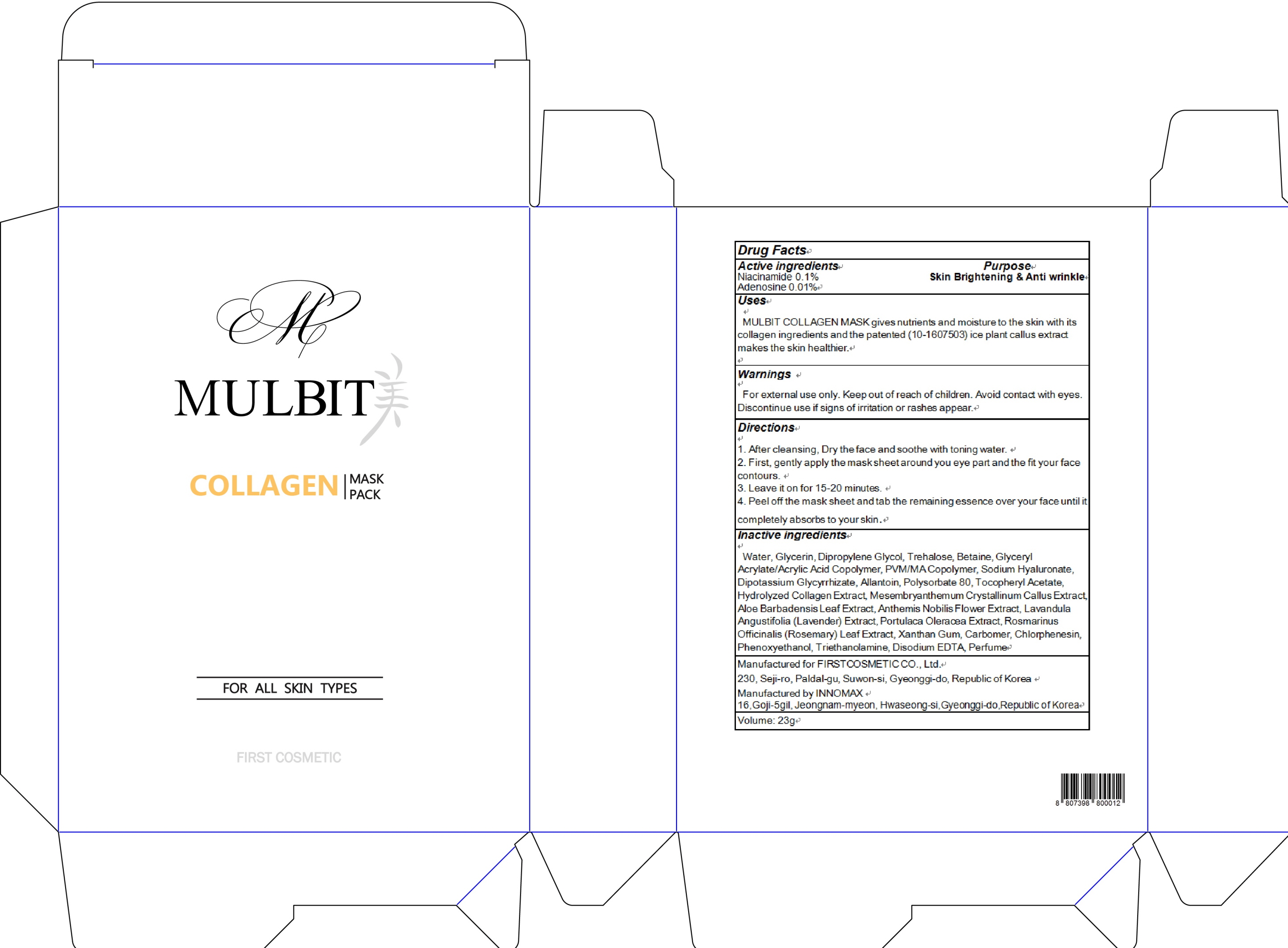 DRUG LABEL: MULBIT Collagen Mask Pack
NDC: 71635-030 | Form: PATCH
Manufacturer: First Cosmetic Co., Ltd
Category: otc | Type: HUMAN OTC DRUG LABEL
Date: 20171020

ACTIVE INGREDIENTS: Niacinamide 0.02 g/23 g; Adenosine 0.002 g/23 g
INACTIVE INGREDIENTS: Water; Glycerin

ACTIVE INGREDIENT

Active ingredients: Niacinamide 0.1%, Adenosine 0.01%

INACTIVE INGREDIENT

Inactive ingredients: Water, Glycerin, Dipropylene Glycol, Trehalose, Betaine, Glyceryl Acrylate/Acrylic Acid Copolymer, PVM/MA Copolymer, Sodium Hyaluronate, Dipotassium Glycyrrhizate, Allantoin, Polysorbate 80, Tocopheryl Acetate, Hydrolyzed Collagen Extract, Mesembryanthemum Crystallinum Callus Extract, Aloe Barbadensis Leaf Extract, Anthemis Nobilis Flower Extract, Lavandula Angustifolia (Lavender) Extract, Portulaca Oleracea Extract, Rosmarinus Officinalis (Rosemary) Leaf Extract, Xanthan Gum, Carbomer, Chlorphenesin, Phenoxyethanol, Triethanolamine, Disodium EDTA, Perfume

PURPOSE

Purpose: Skin Brightening & Anti wrinkle

WARNINGS

Warnings: For external use only. Keep out of reach of children. Avoid contact with eyes. Discontinue use if signs of irritation or rashes appear.

KEEP OUT OF REACH OF CHILDREN

Uses

Uses: MULBIT COLLAGEN MASK gives nutrients and moisture to the skin with its collagen ingredients and the patented (10-1607503) ice plant callus extract makes the skin healthier.

Directions

Directions: 1. After cleansing, dry the face and soothe with toning water. 2. First, gently apply the mask sheet around you eye part and the fit your face contours. 3. Leave it on for 15-20 minutes. 4. Peel off the mask sheet and tab the remaining essence over your face until it completely absorbs to your skin.